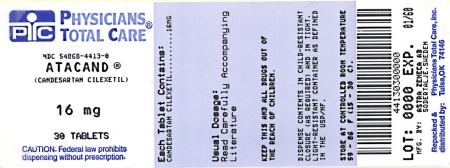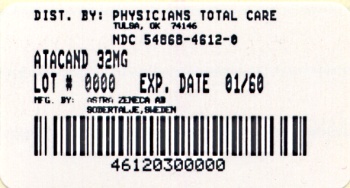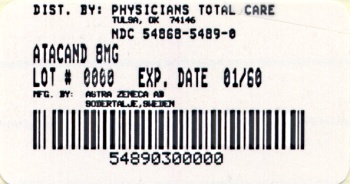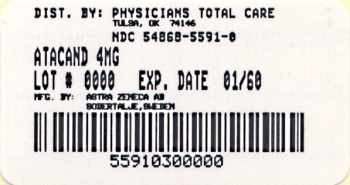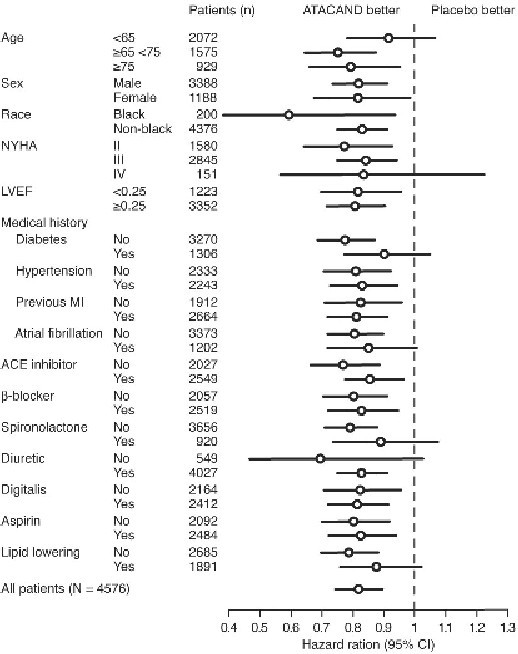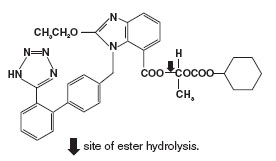 DRUG LABEL: ATACAND
NDC: 54868-5591 | Form: TABLET
Manufacturer: Physicians Total Care, Inc.
Category: prescription | Type: HUMAN PRESCRIPTION DRUG LABEL
Date: 20130812

ACTIVE INGREDIENTS: CANDESARTAN CILEXETIL 4 mg/1 1
INACTIVE INGREDIENTS: POLYETHYLENE GLYCOLS; HYDROXYPROPYL CELLULOSE; LACTOSE MONOHYDRATE; STARCH, CORN; CARBOXYMETHYLCELLULOSE CALCIUM; MAGNESIUM STEARATE; FERRIC OXIDE RED

HIGHLIGHTS OF PRESCRIBING INFORMATION

These highlights do not include all the information needed to use ATACAND safely and effectively. See full prescribing information for ATACAND.
ATACAND® (candesartan cilexetil) TABLETS
INITIAL U.S. APPROVAL: 1998

WARNING: USE IN PREGNANCY: See Full Prescribing Information for complete boxed warning.

When used in pregnancy during the second and third trimesters, drugs that act directly on the renin-angiotensin system can cause injury and even death to the developing fetus. When pregnancy is detected, ATACAND should be discontinued as soon as possible. See WARNINGS AND PRECAUTIONS, Fetal/Neonatal Morbidity and Mortality (5.1).

1 INDICATIONS AND USAGE

ATACAND is an angiotensin II receptor blocker (ARB) indicated for:

· Treatment of hypertension in adults and children 1 to < 17 years of age (1.1).

· Treatment of heart failure (NYHA class II-IV); ATACAND reduces cardiovascular death and heart failure hospitalization (1.2).

2 DOSAGE AND ADMINISTRATION

 | Starting Dose | Dose Range | Target Maintenance Dose
Adult Hypertension (2.1) | 16 mg tablet once daily | 8 - 32 mg tablet total daily dose | –
Pediatric Hypertension (1 to < 6 years) (2.2) | 0.20 mg/kg oral suspension once daily | 0.05 - 0.4 mg/kg oral suspension once daily or consider divided dose | -
Pediatric Hypertension (6 to < 17 years) (2.2) | < 50 kg 4 – 8 mg tablet once daily; > 50 kg 8 – 16 mg tablet once daily | < 50 kg 4 – 16 mg tablet once daily or consider divided dose; > 50 kg 4 – 32 mg tablet once daily or consider divided dose | –
Adult Heart Failure (2.3) | 4 mg tablet once daily |  | 32 mg tablet once daily

3 DOSAGE FORMS and STRENGTHS

Tablets 4 mg, 8 mg, 16 mg, 32 mg (3).

4 CONTRAINDICATIONS

Known hypersensitivity to product components (4).

5 WARNINGS AND PRECAUTIONS

· Avoid fetal (in utero) and neonatal exposure (5.1).

· Children < 1 year of age must not receive ATACAND for hypertension (5.2).

· Observe for signs and symptoms of hypotension (5.3).

· Use with caution in patients with impaired hepatic (5.4) or renal (5.5) function.

· Hyperkalemia may occur in heart failure patients treated with ATACAND (5.6).

6 ADVERSE REACTIONS

· Most common adverse reactions which caused adult patients to discontinue therapy for:

· Hypertension were headache (0.6%) and dizziness (0.3%) (6.1).

· Heart Failure were hypotension (4.1%) (5.3), abnormal renal function (6.3%) (5.5), and hyperkalemia (2.4%) (5.6).

· Most common adverse reactions (incidence ≥ 2% and greater than placebo) are back pain, dizziness, upper respiratory tract infection, pharyngitis and rhinitis (6.1).

To report SUSPECTED ADVERSE REACTIONS contact AstraZeneca at 1–800–236–9933 or FDA at 1-800-FDA-1088 or www.fda.gov/medwatch.

7 DRUG INTERACTIONS

· Lithium: Reversible increases in serum lithium concentrations and toxicity (7).

· NSAIDS use may lead to increased risk of renal impairment and loss of antihypertensive effect (7).

8 USE IN SPECIFIC POPULATIONS

· Nursing Mothers: Either nursing or drug should be discontinued (8.3).

· Pediatrics: Children < 1 year of age must not receive ATACAND for hypertension (5.2). Inhibitors of the renin-angiotensin system can cause renal abnormalities in neonatal animals (12.3).

· Geriatrics: No overall difference in efficacy or safety vs. younger adult patients, but greater sensitivity of some older individuals cannot be ruled out (8.5).

FULL PRESCRIBING INFORMATION

Warning Use in Pregnancy

When used in pregnancy during the second and third trimesters, drugs that act directly on the renin-angiotensin system can cause injury and even death to the developing fetus. When pregnancy is detected, ATACAND should be discontinued as soon as possible [see WARNINGS AND PRECAUTIONS, Fetal/Neonatal Morbidity and Mortality (5.1)].

1 INDICATIONS AND USAGE

1.1 Hypertension

ATACAND is indicated for the treatment of hypertension in adults and children 1 to < 17 years of age. It may be used alone or in combination with other antihypertensive agents.

1.2 Heart Failure

ATACAND is indicated for the treatment of heart failure (NYHA class II-IV) in adults with left ventricular systolic dysfunction (ejection fraction ≤ 40%) to reduce cardiovascular death and to reduce heart failure hospitalizations [see CLINICAL STUDIES (14.2)]. ATACAND also has an added effect on these outcomes when used with an ACE inhibitor.

2 DOSAGE AND ADMINISTRATION

2.1 Adult Hypertension

Dosage must be individualized. Blood pressure response is dose related over the range of 2 to 32 mg. The usual recommended starting dose of ATACAND is 16 mg once daily when it is used as monotherapy in patients who are not volume depleted. ATACAND can be administered once or twice daily with total daily doses ranging from 8 mg to 32 mg. Larger doses do not appear to have a greater effect, and there is relatively little experience with such doses. Most of the antihypertensive effect is present within 2 weeks, and maximal blood pressure reduction is generally obtained within 4 to 6 weeks of treatment with ATACAND.

No initial dosage adjustment is necessary for elderly patients, for patients with mildly impaired renal function, or for patients with mildly impaired hepatic function [see CLINICAL PHARMACOLOGY (12.3)]. In patients with moderate hepatic impairment, consideration should be given to initiation of ATACAND at a lower dose [see CLINICAL PHARMACOLOGY (12.3)]. For patients with possible depletion of intravascular volume (eg, patients treated with diuretics, particularly those with impaired renal function), ATACAND should be initiated under close medical supervision and consideration should be given to administration of a lower dose [see WARNINGS AND PRECAUTIONS (5.3)].

ATACAND may be administered with or without food.

If blood pressure is not controlled by ATACAND alone, a diuretic may be added. ATACAND may be administered with other antihypertensive agents.

2.2 Pediatric Hypertension 1 to < 17 Years of age

ATACAND may be administered once daily or divided into two equal doses. Adjust the dosage according to blood pressure response. For patients with possible depletion of intravascular volume (e.g., patients treated with diuretics, particularly those with impaired renal function), initiate ATACAND under close medical supervision and consider administration of a lower dose [see WARNINGS AND PRECAUTIONS (5.3)].

Children 1 to < 6 years of age:

The dose range is 0.05 to 0.4 mg/kg per day. The recommended starting dose is 0.20 mg/kg (oral suspension).

Children 6 to < 17 years of age:

For those less than 50 kg, the dose range is 2 to 16 mg per day. The recommended starting dose is 4 to 8 mg.

For those greater than 50 kg, the dose range is 4 to 32 mg per day. The recommended starting dose is 8 to 16 mg.

Doses above 0.4 mg/kg (1 to < 6 year olds) or 32 mg (6 to < 17 year olds) have not been studied in pediatric patients [see CLINICAL STUDIES (14.1)].

An antihypertensive effect is usually present within 2 weeks, with full effect generally obtained within 4 weeks of treatment with ATACAND.

Children < 1 year of age must not receive ATACAND for hypertension.

All pediatric patients with a glomerular filtration rate less than 30 ml/min/1.73m^2 should not receive ATACAND since ATACAND has not been studied in this population [see WARNINGS AND PRECAUTIONS (5.2)].

For children who cannot swallow tablets, an oral suspension may be substituted [see Preparation of Oral Suspension].

Preparation of Oral Suspension:

ATACAND oral suspension can be prepared in concentrations within the range of 0.1 to 2.0 mg/mL. Typically, a concentration of 1 mg/mL will be suitable for the prescribed dose. Any strength of ATACAND tablets can be used in the preparation of the suspension.

Follow the steps below for preparation of the suspension. The number of tablets and volume of vehicle specified below will yield 160 mL of a 1 mg/mL suspension.

· Prepare the vehicle by adding equal volumes of *Ora-Plus® (80 mL) and *Ora-Sweet SF® (80 mL) or, alternatively, use *,†Ora-Blend SF® (160 mL).

· Add a small amount of vehicle to the required number of ATACAND tablets (five 32 mg tablets) and grind into a smooth paste using a mortar and pestle.

· Add the paste to a preparation vessel of suitable size.

· Rinse the mortar and pestle clean using the vehicle and add this to the vessel. Repeat, if necessary.

· Prepare the final volume by adding the remaining vehicle.

· Mix thoroughly.

· Dispense into suitably sized amber PET bottles.

· Label with an expiry date of 100 days and include the following instructions:

Store at room temperature (below 30°C/86°F). Use within 30 days after first opening. Do not use after the expiry date stated on the bottle.

Do not freeze.

Shake well before each use.

*Ora-Plus®, Ora-Sweet SF®, and Ora-Blend SF® are registered trademarks of Paddock Laboratories, Inc.

†Supplied as a 50/50% pre-mix of Ora-Plus® and Ora-Sweet SF®.

2.3 Adult Heart Failure

The recommended initial dose for treating heart failure is 4 mg once daily. The target dose is 32 mg once daily, which is achieved by doubling the dose at approximately 2-week intervals, as tolerated by the patient.

3 DOSAGE FORMS and STRENGTHS

4 mg are white to off-white, circular/biconvex-shaped, non-film-coated scored tablets, coded ACF on one side and 004 on the other.

8 mg are light pink, circular/biconvex-shaped, non-film-coated scored tablets, coded ACG on one side and 008 on the other.

16 mg are pink, circular/biconvex-shaped, non-film-coated scored tablets, coded ACH on one side and 016 on the other.

32 mg are pink, circular/biconvex-shaped, non-film-coated scored tablets, coded ACL on one side and 032 on the other.

4 CONTRAINDICATIONS

ATACAND is contraindicated in patients who are hypersensitive to any component of this product.

5 WARNINGS AND PRECAUTIONS

5.1 Fetal/Neonatal Morbidity and Mortality

Drugs that act directly on the renin-angiotensin system can cause fetal and neonatal morbidity and death when administered to pregnant women. Several dozen cases have been reported in the world literature in patients who were taking angiotensin-converting enzyme inhibitors. Post-marketing experience has identified reports of fetal and neonatal toxicity in babies born to women treated with ATACAND during pregnancy. When pregnancy is detected, ATACAND should be discontinued as soon as possible.

The use of drugs that act directly on the renin-angiotensin system during the second and third trimesters of pregnancy has been associated with fetal and neonatal injury, including hypotension, neonatal skull hypoplasia, anuria, reversible or irreversible renal failure, and death. Oligohydramnios has also been reported, presumably resulting from decreased fetal renal function; oligohydramnios in this setting has been associated with fetal limb contractures, craniofacial deformation, and hypoplastic lung development. Prematurity, intrauterine growth retardation, and patent ductus arteriosus have also been reported, although it is not clear whether these occurrences were due to exposure to the drug.

These adverse effects do not appear to have resulted from intrauterine drug exposure that has been limited to the first trimester. Mothers whose embryos and fetuses are exposed to an angiotensin II receptor antagonist only during the first trimester should be so informed. Nonetheless, when patients become pregnant, physicians should have the patient discontinue the use of ATACAND as soon as possible.

Rarely (probably less often than once in every thousand pregnancies), no alternative to a drug acting on the renin-angiotensin system will be found. In these rare cases, the mothers should be apprised of the potential hazards to their fetuses, and serial ultrasound examinations should be performed to assess the intra-amniotic environment.

If oligohydramnios is observed, ATACAND should be discontinued unless it is considered life saving for the mother. Contraction stress testing (CST), a nonstress test (NST), or biophysical profiling (BPP) may be appropriate, depending upon the week of pregnancy. Patients and physicians should be aware, however, that oligohydramnios may not appear until after the fetus has sustained irreversible injury.

Infants with histories of in utero exposure to an angiotensin II receptor antagonist should be closely observed for hypotension, oliguria, and hyperkalemia. If oliguria occurs, attention should be directed toward support of blood pressure and renal perfusion. Exchange transfusion or dialysis may be required as means of reversing hypotension and/or substituting for disordered renal function.

Oral doses ≥10 mg of candesartan cilexetil/kg/day administered to pregnant rats during late gestation and continued through lactation were associated with reduced survival and an increased incidence of hydronephrosis in the offspring. The 10-mg/kg/day dose in rats is approximately 2.8 times the maximum recommended daily human dose (MRHD) of 32 mg on a mg/m^2 basis (comparison assumes human body weight of 50 kg). Candesartan cilexetil given to pregnant rabbits at an oral dose of 3 mg/kg/day (approximately 1.7 times the MRHD on a mg/m^2 basis) caused maternal toxicity (decreased body weight and death) but, in surviving dams, had no adverse effects on fetal survival, fetal weight, or external, visceral, or skeletal development. No maternal toxicity or adverse effects on fetal development were observed when oral doses up to 1000 mg of candesartan cilexetil/kg/day (approximately 138 times the MRHD on a mg/m^2 basis) were administered to pregnant mice.

5.2 Morbidity in Infants

Children < 1 year of age must not receive ATACAND for hypertension. The consequences of administering drugs that act directly on the renin-angiotensin system (RAS) can have effects on the development of immature kidneys.

5.3 Hypotension

In adult or children patients with an activated renin-angiotensin system, such as volume- and/or salt-depleted patients (eg, those being treated with diuretics), symptomatic hypotension may occur. These conditions should be corrected prior to administration of ATACAND, or the treatment should start under close medical supervision [see DOSAGE AND ADMINISTRATION (2.1)].

If hypotension occurs, the patients should be placed in the supine position and, if necessary, given an intravenous infusion of normal saline. A transient hypotensive response is not a contraindication to further treatment which usually can be continued without difficulty once the blood pressure has stabilized.

Caution should be observed when initiating therapy in patients with heart failure. Patients with heart failure given ATACAND commonly have some reduction in blood pressure. In patients with symptomatic hypotension this may require temporarily reducing the dose of ATACAND, or diuretic, or both, and volume repletion. In the CHARM program, hypotension was reported in 18.8% of patients on ATACAND versus 9.8% of patients on placebo. The incidence of hypotension leading to drug discontinuation in ATACAND-treated patients was 4.1% compared with 2.0% in placebo-treated patients.

Monitoring of blood pressure is recommended during dose escalation and periodically thereafter.

Major Surgery/Anesthesia

Hypotension may occur during major surgery and anesthesia in patients treated with angiotensin II receptor antagonists, including ATACAND, due to blockade of the renin-angiotensin system. Very rarely, hypotension may be severe such that it may warrant the use of intravenous fluids and/or vasopressors.

5.4 Impaired Hepatic Function

Based on pharmacokinetic data which demonstrate significant increases in candesartan AUC and Cmax in patients with moderate hepatic impairment, a lower initiating dose should be considered for patients with moderate hepatic impairment [see CLINICAL PHARMACOLOGY (12.3)].

5.5 Renal Function Deterioration

As a consequence of inhibiting the renin-angiotensin-aldosterone system, changes in renal function may be anticipated in some individuals treated with ATACAND. In patients whose renal function may depend upon the activity of the renin-angiotensin-aldosterone system (eg, patients with severe heart failure), treatment with angiotensin-converting enzyme inhibitors and angiotensin receptor antagonists has been associated with oliguria and/or progressive azotemia and (rarely) with acute renal failure and/or death. Similar results may be anticipated in patients treated with ATACAND [see CLINICAL PHARMACOLOGY (12.3)].

In studies of ACE inhibitors in patients with unilateral or bilateral renal artery stenosis, increases in serum creatinine or blood urea nitrogen (BUN) have been reported. There has been no long-term use of ATACAND in patients with unilateral or bilateral renal artery stenosis, but similar results may be expected.

In heart failure patients treated with ATACAND, increases in serum creatinine may occur. Dosage reduction or discontinuation of the diuretic or ATACAND, and volume repletion may be required. In the CHARM program, the incidence of abnormal renal function (e.g., creatinine increase) was 12.5% in patients treated with ATACAND versus 6.3% in patients treated with placebo. The incidence of abnormal renal function (eg, creatinine increase) leading to drug discontinuation in ATACAND-treated patients was 6.3% compared with 2.9% in placebo-treated patients. Evaluation of patients with heart failure should always include assessment of renal function and volume status. Monitoring of serum creatinine is recommended during dose escalation and periodically thereafter.

Pediatrics - ATACAND has not been studied in children with estimated glomerular filtration rate < 30 mL/min/1.73m^2.

5.6 Hyperkalemia

In heart failure patients treated with ATACAND, hyperkalemia may occur, especially when taken concomitantly with ACE inhibitors and potassium-sparing diuretics such as spironolactone. In the CHARM program, the incidence of hyperkalemia was 6.3% in patients treated with ATACAND versus 2.1% in patients treated with placebo. The incidence of hyperkalemia leading to drug discontinuation in ATACAND-treated patients was 2.4% compared with 0.6% in placebo-treated patients. During treatment with ATACAND in patients with heart failure, monitoring of serum potassium is recommended during dose escalation and periodically thereafter.

6 ADVERSE REACTIONS

6.1 Clinical Studies Experience

Because clinical studies are conducted under widely varying conditions, adverse reaction rates observed in the clinical studies of a drug cannot be directly compared to rates in the clinical studies of another drug and may not reflect the rates observed in practice.

Adult Hypertension

ATACAND has been evaluated for safety in more than 3600 patients/subjects, including more than 3200 patients treated for hypertension. About 600 of these patients were studied for at least 6 months and about 200 for at least 1 year. In general, treatment with ATACAND was well tolerated. The overall incidence of adverse events reported with ATACAND was similar to placebo.

The rate of withdrawals due to adverse events in all trials in patients (7510 total) was 3.3% (ie, 108 of 3260) of patients treated with ATACAND as monotherapy and 3.5% (ie, 39 of 1106) of patients treated with placebo. In placebo-controlled trials, discontinuation of therapy due to clinical adverse events occurred in 2.4% (ie, 57 of 2350) of patients treated with ATACAND and 3.4% (ie, 35 of 1027) of patients treated with placebo.

The most common reasons for discontinuation of therapy with ATACAND were headache (0.6%) and dizziness (0.3%).

The adverse events that occurred in placebo-controlled clinical trials in at least 1% of patients treated with ATACAND and at a higher incidence in candesartan cilexetil (n = 2350) than placebo (n = 1027) patients included back pain (3% vs. 2%), dizziness (4% vs. 3%), upper respiratory tract infection (6% vs. 4%), pharyngitis (2% vs. 1%), and rhinitis (2% vs. 1%).

The following adverse events occurred in placebo-controlled clinical trials at a more than 1% rate but at about the same or greater incidence in patients receiving placebo compared to ATACAND: fatigue, peripheral edema, chest pain, headache, bronchitis, coughing, sinusitis, nausea, abdominal pain, diarrhea, vomiting, arthralgia, albuminuria.

Other potentially important adverse events that have been reported, whether or not attributed to treatment, with an incidence of 0.5% or greater from the 3260 patients worldwide treated in clinical trials with ATACAND are listed below. It cannot be determined whether these events were causally related to ATACAND. Body as a Whole: asthenia, fever; Central and Peripheral Nervous System: paresthesia, vertigo; Gastrointestinal System Disorder: dyspepsia, gastroenteritis; Heart Rate and Rhythm Disorders: tachycardia, palpitation; Metabolic and Nutritional Disorders: creatine phosphokinase increased, hyperglycemia, hypertriglyceridemia, hyperuricemia; Musculoskeletal System Disorders: myalgia; Platelet/Bleeding-Clotting Disorders: epistaxis; Psychiatric Disorders: anxiety, depression, somnolence; Respiratory System Disorders: dyspnea; Skin and Appendages Disorders: rash, sweating increased; Urinary System Disorders: hematuria.

Other reported events seen less frequently included angina pectoris, myocardial infarction, and angioedema.

Adverse events occurred at about the same rates in men and women, older and younger patients, and black and non-black patients.

Pediatric Hypertension

Among children in clinical studies, 1 in 93 children age 1 to < 6 and 3 in 240 age 6 to < 17 experienced worsening renal disease. The association between candesartan and exacerbation of the underlying condition could not be excluded.

Heart Failure

The adverse event profile of ATACAND in adult heart failure patients was consistent with the pharmacology of the drug and the health status of the patients. In the CHARM program, comparing ATACAND in total daily doses up to 32 mg once daily (n=3803) with placebo (n=3796), 21.0% of patients discontinued ATACAND for adverse events vs. 16.1% of placebo patients.

6.2 Postmarketing Experience

The following adverse reactions were identified during post-approval use of ATACAND. Because these reactions are reported voluntarily from a population of uncertain size, it is not always possible to reliably estimate their frequency or establish a causal relationship to drug exposure.

The following have been very rarely reported in post-marketing experience:

Digestive: Abnormal hepatic function and hepatitis.

Hematologic: Neutropenia, leukopenia, and agranulocytosis.

Metabolic and Nutritional Disorders: hyperkalemia, hyponatremia.

Renal: renal impairment, renal failure.

Skin and Appendages Disorders: Pruritus and urticaria.

Rare reports of rhabdomyolysis have been reported in patients receiving angiotensin II receptor blockers.

6.3 Laboratory Test Findings

Hypertension

In controlled clinical trials, clinically important changes in standard laboratory parameters were rarely associated with the administration of ATACAND.

Creatinine, Blood Urea Nitrogen

Minor increases in blood urea nitrogen (BUN) and serum creatinine were observed infrequently.

Hyperuricemia

Hyperuricemia was rarely found (19 or 0.6% of 3260 patients treated with ATACAND and 5 or 0.5% of 1106 patients treated with placebo).

Hemoglobin and Hematocrit

Small decreases in hemoglobin and hematocrit (mean decreases of approximately 0.2 grams/dL and 0.5 volume percent, respectively) were observed in patients treated with ATACAND alone but were rarely of clinical importance. Anemia, leukopenia, and thrombocytopenia were associated with withdrawal of one patient each from clinical trials.

Potassium

A small increase (mean increase of 0.1 mEq/L) was observed in patients treated with ATACAND alone but was rarely of clinical importance. One patient from a congestive heart failure trial was withdrawn for hyperkalemia (serum potassium = 7.5 mEq/L). This patient was also receiving spironolactone [see WARNINGS AND PRECAUTIONS (5.6)].

Liver Function Tests

Elevations of liver enzymes and/or serum bilirubin were observed infrequently. Five patients assigned to ATACAND in clinical trials were withdrawn because of abnormal liver chemistries. All had elevated transaminases. Two had mildly elevated total bilirubin, but one of these patients was diagnosed with Hepatitis A.

Heart Failure

In the CHARM program, small increases in serum creatinine (mean increase 0.2 mg/dL in candesartan-treated patients and 0.1 mg/dL in placebo-treated patients) and serum potassium (mean increase 0.15 mEq/L in ATACAND-treated patients and 0.02 mEq/L in placebo-treated patients), and small decreases in hemoglobin (mean decrease 0.5 gm/dL in ATACAND-treated patients and 0.3 gm/dL in placebo-treated patients) and hematocrit (mean decrease 1.6% in ATACAND-treated patients and 0.9% in placebo-treated patients) were observed.

7 DRUG INTERACTIONS

No significant drug interactions have been reported in studies of candesartan cilexetil given with other drugs such as glyburide, nifedipine, digoxin, warfarin, hydrochlorothiazide, and oral contraceptives in healthy volunteers, or given with enalapril to patients with heart failure (NYHA class II and III). Because candesartan is not significantly metabolized by the cytochrome P450 system and at therapeutic concentrations has no effects on P450 enzymes, interactions with drugs that inhibit or are metabolized by those enzymes would not be expected.

Non-Steroidal Anti-Inflammatory Agents including Selective Cyclooxygenase-2 Inhibitors (COX-2 Inhibitors). In patients who are elderly, volume-depleted (including those on diuretic therapy), or with compromised renal function, co-administration of NSAIDs, including selective COX-2 inhibitors, with angiotensin II receptor antagonists, including candesartan, may result in deterioration of renal function, including possible acute renal failure. These effects are usually reversible. Monitor renal function periodically in patients receiving candesartan and NSAID therapy.

The antihypertensive effect of angiotensin II receptor antagonists, including candesartan may be attenuated by NSAIDs including selective COX-2 inhibitors.

Lithium

Reversible increases in serum lithium concentrations and toxicity have been reported during concomitant administration of lithium with ACE inhibitors, and with some angiotensin II receptor antagonists. An increase in serum lithium concentration has been reported during concomitant administration of lithium with ATACAND, so careful monitoring of serum lithium levels is recommended during concomitant use.

8 USE IN SPECIFIC POPULATIONS

8.1 Pregnancy

Pregnancy Categories C (first trimester) and D (second and third trimesters) [see WARNINGS AND PRECAUTIONS (5.1)].

8.2 Labor and Delivery

The effect of ATACAND on labor and delivery in humans is unknown [see WARNINGS AND PRECAUTIONS (5.1)].

8.3 Nursing Mothers

It is not known whether candesartan is excreted in human milk, but candesartan has been shown to be present in rat milk. Because of the potential for adverse effects on the nursing infant, a decision should be made whether to discontinue nursing or discontinue ATACAND, taking into account the importance of the drug to the mother.

8.4 Pediatric Use

The antihypertensive effects of ATACAND were evaluated in hypertensive children 1 to < 17 years of age in randomized, double-blind clinical studies [see CLINICAL STUDIES (14.1)]. The pharmacokinetics of ATACAND have been evaluated in pediatric patients 1 to < 17 years of age [see Pharmacokinetics (12.3)].

Children < 1 year of age must not receive ATACAND for hypertension [see WARNINGS AND PRECAUTIONS (5.2)].

8.5 Geriatric Use

Hypertension

Of the total number of subjects in clinical studies of ATACAND, 21% (683/3260) were 65 and over, while 3% (87/3260) were 75 and over. No overall differences in safety or effectiveness were observed between these subjects and younger adult subjects, and other reported clinical experience has not identified differences in responses between the elderly and younger patients, but greater sensitivity of some older individuals cannot be ruled out. In a placebo-controlled trial of about 200 elderly hypertensive patients (ages 65 to 87 years), administration of candesartan cilexetil was well tolerated and lowered blood pressure by about 12/6 mm Hg more than placebo.

Heart Failure

Of the 7599 patients with heart failure in the CHARM program, 4343 (57%) were age 65 years or older and 1736 (23%) were 75 years or older. In patients ≥ 75 years of age, the incidence of drug discontinuations due to adverse events was higher for those treated with ATACAND or placebo compared with patients <75 years of age. In these patients, the most common adverse events leading to drug discontinuation at an incidence of at least 3%, and more frequent with ATACAND than placebo, were abnormal renal function (7.9% vs. 4.0%), hypotension (5.2% vs. 3.2%) and hyperkalemia (4.2% vs. 0.9%). In addition to monitoring of serum creatinine, potassium, and blood pressure during dose escalation and periodically thereafter, greater sensitivity of some older individuals with heart failure must be considered.

10 OVERDOSAGE

No lethality was observed in acute toxicity studies in mice, rats, and dogs given single oral doses of up to 2000 mg/kg of candesartan cilexetil. In mice given single oral doses of the primary metabolite, candesartan, the minimum lethal dose was greater than 1000 mg/kg but less than 2000 mg/kg.

The most likely manifestation of overdosage with ATACAND would be hypotension, dizziness, and tachycardia; bradycardia could occur from parasympathetic (vagal) stimulation. If symptomatic hypotension should occur, supportive treatment should be instituted.

Candesartan cannot be removed by hemodialysis.

Treatment: To obtain up-to-date information about the treatment of overdose, consult your Regional Poison Control Center. Telephone numbers of certified poison control centers are listed in the Physicians’ Desk Reference (PDR). In managing overdose, consider the possibilities of multiple-drug overdoses, drug-drug interactions, and altered pharmacokinetics in your patient.

11 DESCRIPTION

ATACAND (candesartan cilexetil), a prodrug, is hydrolyzed to candesartan during absorption from the gastrointestinal tract. Candesartan is a selective AT1 subtype angiotensin II receptor antagonist.

Candesartan cilexetil, a nonpeptide, is chemically described as (±)-1-Hydroxyethyl 2-ethoxy-1-[p-(o-1H-tetrazol-5-ylphenyl)benzyl]-7-benzimidazolecarboxylate, cyclohexyl carbonate (ester).

Its empirical formula is C33H34N6O6, and its structural formula is:

Candesartan cilexetil is a white to off-white powder with a molecular weight of 610.67. It is practically insoluble in water and sparingly soluble in methanol. Candesartan cilexetil is a racemic mixture containing one chiral center at the cyclohexyloxycarbonyloxy ethyl ester group. Following oral administration, candesartan cilexetil undergoes hydrolysis at the ester link to form the active drug, candesartan, which is achiral.

ATACAND is available for oral use as tablets containing either 4 mg, 8 mg, 16 mg, or 32 mg of candesartan cilexetil and the following inactive ingredients: hydroxypropyl cellulose, polyethylene glycol, lactose, corn starch, carboxymethylcellulose calcium, and magnesium stearate. Ferric oxide (reddish brown) is added to the 8-mg, 16-mg, and 32-mg tablets as a colorant.

12 CLINICAL PHARMACOLOGY

12.1 Mechanism of Action

Angiotensin II is formed from angiotensin I in a reaction catalyzed by angiotensin-converting enzyme (ACE, kininase II). Angiotensin II is the principal pressor agent of the renin-angiotensin system, with effects that include vasoconstriction, stimulation of synthesis and release of aldosterone, cardiac stimulation, and renal reabsorption of sodium. Candesartan blocks the vasoconstrictor and aldosterone-secreting effects of angiotensin II by selectively blocking the binding of angiotensin II to the AT1 receptor in many tissues, such as vascular smooth muscle and the adrenal gland. Its action is, therefore, independent of the pathways for angiotensin II synthesis.

There is also an AT2 receptor found in many tissues, but AT2 is not known to be associated with cardiovascular homeostasis. Candesartan has much greater affinity (>10,000-fold) for the AT1 receptor than for the AT2 receptor.

Blockade of the renin-angiotensin system with ACE inhibitors, which inhibit the biosynthesis of angiotensin II from angiotensin I, is widely used in the treatment of hypertension. ACE inhibitors also inhibit the degradation of bradykinin, a reaction also catalyzed by ACE. Because candesartan does not inhibit ACE (kininase II), it does not affect the response to bradykinin. Whether this difference has clinical relevance is not yet known. Candesartan does not bind to or block other hormone receptors or ion channels known to be important in cardiovascular regulation.

Blockade of the angiotensin II receptor inhibits the negative regulatory feedback of angiotensin II on renin secretion, but the resulting increased plasma renin activity and angiotensin II circulating levels do not overcome the effect of candesartan on blood pressure.

12.2 Pharmacodynamics

Candesartan inhibits the pressor effects of angiotensin II infusion in a dose-dependent manner. After 1 week of once daily dosing with 8 mg of candesartan cilexetil, the pressor effect was inhibited by approximately 90% at peak with approximately 50% inhibition persisting for 24 hours.

Plasma concentrations of angiotensin I and angiotensin II, and plasma renin activity (PRA), increased in a dose-dependent manner after single and repeated administration of candesartan cilexetil to healthy subjects, hypertensive, and heart failure patients. ACE activity was not altered in healthy subjects after repeated candesartan cilexetil administration. The once-daily administration of up to 16 mg of candesartan cilexetil to healthy subjects did not influence plasma aldosterone concentrations, but a decrease in the plasma concentration of aldosterone was observed when 32 mg of candesartan cilexetil was administered to hypertensive patients. In spite of the effect of candesartan cilexetil on aldosterone secretion, very little effect on serum potassium was observed.

Hypertension

Adults

In multiple-dose studies with hypertensive patients, there were no clinically significant changes in metabolic function, including serum levels of total cholesterol, triglycerides, glucose, or uric acid. In a 12-week study of 161 patients with non-insulin-dependent (type 2) diabetes mellitus and hypertension, there was no change in the level of HbA1c.

Heart Failure

In heart failure patients, candesartan ≥ 8 mg resulted in decreases in systemic vascular resistance and pulmonary capillary wedge pressure.

12.3 Pharmacokinetics

Distribution

The volume of distribution of candesartan is 0.13 L/kg. Candesartan is highly bound to plasma proteins (>99%) and does not penetrate red blood cells. The protein binding is constant at candesartan plasma concentrations well above the range achieved with recommended doses. In rats, it has been demonstrated that candesartan crosses the blood-brain barrier poorly, if at all. It has also been demonstrated in rats that candesartan passes across the placental barrier and is distributed in the fetus.

Metabolism and Excretion

Total plasma clearance of candesartan is 0.37 mL/min/kg, with a renal clearance of 0.19 mL/min/kg. When candesartan is administered orally, about 26% of the dose is excreted unchanged in urine. Following an oral dose of ^14C-labeled candesartan cilexetil, approximately 33% of radioactivity is recovered in urine and approximately 67% in feces. Following an intravenous dose of ^14C-labeled candesartan, approximately 59% of radioactivity is recovered in urine and approximately 36% in feces. Biliary excretion contributes to the elimination of candesartan.

Adults

Candesartan cilexetil is rapidly and completely bioactivated by ester hydrolysis during absorption from the gastrointestinal tract to candesartan, a selective AT1 subtype angiotensin II receptor antagonist. Candesartan is mainly excreted unchanged in urine and feces (via bile). It undergoes minor hepatic metabolism by O-deethylation to an inactive metabolite. The elimination half-life of candesartan is approximately 9 hours. After single and repeated administration, the pharmacokinetics of candesartan are linear for oral doses up to 32 mg of candesartan cilexetil. Candesartan and its inactive metabolite do not accumulate in serum upon repeated once-daily dosing.

Following administration of candesartan cilexetil, the absolute bioavailability of candesartan was estimated to be 15%. After tablet ingestion, the peak serum concentration (Cmax) is reached after 3 to 4 hours. Food with a high fat content does not affect the bioavailability of candesartan after candesartan cilexetil administration.

Pediatrics

In children 1 to 17 years of age, plasma levels are greater than 10–fold higher at peak (approximately 4 hours) than 24 hours after a single dose.

Children 1 to < 6 years of age, given 0.2 mg/kg had exposure similar to adults given 8 mg.

Children > 6 years of age had exposure similar to adults given the same dose.

The pharmacokinetics (Cmax and AUC) were not modified by age, sex or body weight.

Candesartan cilexetil pharmacokinetics have not been investigated in pediatric patients less than 1 year of age.

From the dose-ranging studies of candesartan cilexetil, there was a dose related increase in plasma candesartan concentrations.

The renin-angiotensin system (RAS) plays a critical role in kidney development. RAS blockade has been shown to lead to abnormal kidney development in very young mice. Children < 1 year of age must not receive ATACAND. Administering drugs that act directly on the renin-angiotensin system (RAS) can alter normal renal development.

Geriatric and Sex

The pharmacokinetics of candesartan have been studied in the elderly (≥ 65 years) and in both sexes. The plasma concentration of candesartan was higher in the elderly (Cmax was approximately 50% higher, and AUC was approximately 80% higher) compared to younger subjects administered the same dose. The pharmacokinetics of candesartan were linear in the elderly, and candesartan and its inactive metabolite did not accumulate in the serum of these subjects upon repeated, once-daily administration. No initial dosage adjustment is necessary [see DOSAGE AND ADMINISTRATION (2)]. There is no difference in the pharmacokinetics of candesartan between male and female subjects.

Renal Insufficiency

In hypertensive patients with renal insufficiency, serum concentrations of candesartan were elevated. After repeated dosing, the AUC and Cmax were approximately doubled in patients with severe renal impairment (creatinine clearance <30 mL/min/1.73m^2) compared to patients with normal kidney function. The pharmacokinetics of candesartan in hypertensive patients undergoing hemodialysis are similar to those in hypertensive patients with severe renal impairment. Candesartan cannot be removed by hemodialysis. No initial dosage adjustment is necessary in patients with renal insufficiency [see DOSAGE AND ADMINISTRATION (2.1)].

In heart failure patients with renal impairment, AUC0-72h was 36% and 65% higher in mild and moderate renal impairment, respectively. Cmax was 15% and 55% higher in mild and moderate renal impairment, respectively.

Pediatrics:

ATACAND pharmacokinetics have not been determined in children with renal insufficiency.

Hepatic Insufficiency

The pharmacokinetics of candesartan were compared in patients with mild and moderate hepatic impairment to matched healthy volunteers following a single oral dose of 16 mg candesartan cilexetil. The increase in AUC for candesartan was 30% in patients with mild hepatic impairment (Child-Pugh A) and 145% in patients with moderate hepatic impairment (Child-Pugh B). The increase in Cmax for candesartan was 56% in patients with mild hepatic impairment and 73% in patients with moderate hepatic impairment. The pharmacokinetics after candesartan cilexetil administration have not been investigated in patients with severe hepatic impairment. No initial dosage adjustment is necessary in patients with mild hepatic impairment. In hypertensive patients with moderate hepatic impairment, consideration should be given to initiation of ATACAND at a lower dose [see DOSAGE AND ADMINISTRATION (2.1)].

Heart Failure

The pharmacokinetics of candesartan were linear in patients with heart failure (NYHA class II and III) after candesartan cilexetil doses of 4, 8, and 16 mg. After repeated dosing, the AUC was approximately doubled in these patients compared with healthy, younger patients. The pharmacokinetics in heart failure patients is similar to that in healthy elderly volunteers [see DOSAGE AND ADMINISTRATION (2.3)].

13 NONCLINICAL TOXICOLOGY

13.1 Carcinogenesis, Mutagenesis, Impairment of Fertility

There was no evidence of carcinogenicity when candesartan cilexetil was orally administered to mice and rats for up to 104 weeks at doses up to 100 and 1000 mg/kg/day, respectively. Rats received the drug by gavage, whereas mice received the drug by dietary administration. These (maximally-tolerated) doses of candesartan cilexetil provided systemic exposures to candesartan (AUCs) that were, in mice, approximately 7 times and, in rats, more than 70 times the exposure in man at the maximum recommended daily human dose (32 mg).

Candesartan and its O-deethyl metabolite tested positive for genotoxicity in the in vitro Chinese hamster lung (CHL) chromosomal aberration assay. Neither compound tested positive in the Ames microbial mutagenesis assay or the in vitro mouse lymphoma cell assay. Candesartan (but not its O-deethyl metabolite) was also evaluated in vivo in the mouse micronucleus test and in vitro in the Chinese hamster ovary (CHO) gene mutation assay, in both cases with negative results. Candesartan cilexetil was evaluated in the Ames test, the in vitro mouse lymphoma cell and rat hepatocyte unscheduled DNA synthesis assays and the in vivo mouse micronucleus test, in each case with negative results. Candesartan cilexetil was not evaluated in the CHL chromosomal aberration or CHO gene mutation assay.

Fertility and reproductive performance were not affected in studies with male and female rats given oral doses of up to 300 mg/kg/day (83 times the maximum daily human dose of 32 mg on a body surface area basis).

14.1 Hypertension

Adult

The antihypertensive effects of ATACAND were examined in 14 placebo-controlled trials of 4- to 12-weeks duration, primarily at daily doses of 2 to 32 mg per day in patients with baseline diastolic blood pressures of 95 to 114 mm Hg. Most of the trials were of candesartan cilexetil as a single agent, but it was also studied as add-on to hydrochlorothiazide and amlodipine. These studies included a total of 2350 patients randomized to one of several doses of candesartan cilexetil and 1027 to placebo. Except for a study in diabetics, all studies showed significant effects, generally dose related, of 2 to 32 mg on trough (24 hour) systolic and diastolic pressures compared to placebo, with doses of 8 to 32 mg giving effects of about 8-12/4-8 mm Hg. There were no exaggerated first-dose effects in these patients. Most of the antihypertensive effect was seen within 2 weeks of initial dosing and the full effect in 4 weeks. With once-daily dosing, blood pressure effect was maintained over 24 hours, with trough to peak ratios of blood pressure effect generally over 80%. Candesartan cilexetil had an additional blood pressure lowering effect when added to hydrochlorothiazide.

The antihypertensive effects of candesartan cilexetil and losartan potassium at their highest recommended doses administered once— daily were compared in two randomized, double-blind trials. In a total of 1268 patients with mild to moderate hypertension who were not receiving other antihypertensive therapy, candesartan cilexetil 32 mg lowered systolic and diastolic blood pressure by 2 to 3 mm Hg on average more than losartan potassium 100 mg, when measured at the time of either peak or trough effect. The antihypertensive effects of twice daily dosing of either candesartan cilexetil or losartan potassium were not studied.

The antihypertensive effect was similar in men and women and in patients older and younger than 65. Candesartan was effective in reducing blood pressure regardless of race, although the effect was somewhat less in blacks (usually a low-renin population). This has been generally true for angiotensin II antagonists and ACE inhibitors.

In long-term studies of up to 1 year, the antihypertensive effectiveness of candesartan cilexetil was maintained, and there was no rebound after abrupt withdrawal.

There were no changes in the heart rate of patients treated with candesartan cilexetil in controlled trials.

Pediatric

The antihypertensive effects of ATACAND were evaluated in hypertensive children 1 to < 6 years old and 6 to < 17 years of age in two randomized, double-blind multicenter, 4-week dose ranging studies. There were 93 patients 1 to < 6 years of age, 74% of whom had renal disease, that were randomized to receive an oral dose of candesartan cilexetil suspension 0.05, 0.20 or 0.40 mg/kg once daily. The primary method of analysis was slope of the change in systolic blood pressure (SBP) as a function of dose. Since there was no placebo group, the change from baseline likely overestimates the true magnitude of blood pressure effect. Nevertheless, SBP and diastolic blood pressure (DBP) decreased 6.0/5.2 to 12.0/11.1 mmHg from baseline across the three doses of candesartan.

In children 6 to < 17 years, 240 patients were randomized to receive either placebo or low, medium, or high doses of ATACAND in a ratio of 1: 2: 2: 2. For children who weighed < 50 kg the doses of ATACAND were 2, 8, or 16 mg once daily. For those > 50 kg the ATACAND doses were 4, 16 or 32 mg once daily. Those enrolled were 47% Black and 29% were female; mean age +/- SD was 12.9 +/- 2.6 years.

The placebo subtracted effect at trough for sitting systolic blood pressure/sitting diastolic blood pressure for the different doses were from 4.9/3.0 to 7.5/6.2 mmHg.

In children 6 to < 17 years there was a trend for a lesser blood pressure effect for Blacks compared to other patients. There were too few individuals in the age group of 1 - 6 years old to determine whether Blacks respond differently than other patients to ATACAND.

14.2 Heart Failure

Candesartan was studied in two heart failure outcome studies: 1. The Candesartan in Heart failure: Assessment of Reduction in Mortality and morbidity trial in patients intolerant of ACE inhibitors (CHARM–Alternative), 2. CHARM–Added in patients already receiving ACE inhibitors. Both studies were international double-blind, placebo-controlled trials in patients with NYHA class II - IV heart failure and LVEF ≤40%. In both trials, patients were randomized to placebo or ATACAND (initially 4-8 mg once daily, titrated as tolerated to 32 mg once daily) and followed for up to 4 years. Patients with serum creatinine > 3 mg/dL, serum potassium > 5.5 mEq/L, symptomatic hypotension or known bilateral renal artery stenosis were excluded. The primary end point in both trials was time to either cardiovascular death or hospitalization for heart failure.

CHARM–Alternative included 2028 subjects not receiving an ACE inhibitor due to intolerance. The mean age was 67 years and 32% were female, 48% were NYHA II, 49% were NYHA III, 4% were NYHA IV, and the mean ejection fraction was 30%. Sixty-two percent had a history of myocardial infarction, 50% had a history of hypertension, and 27% had diabetes. Concomitant drugs at baseline were diuretics (85%), digoxin (46%), beta-blockers (55%), and spironolactone (24%). The mean daily dose of ATACAND was approximately 23 mg and 59% of subjects on treatment received 32 mg once daily.

After a median follow-up of 34 months, there was a 23% reduction in the risk of cardiovascular death or heart failure hospitalization on ATACAND (p<0.001), with both components contributing to the overall effect (Table 1).

Table 1. CHARM — Alternative: Primary Endpoint and its Components
Endpoint (time to first event) | ATACAND (n= 1013) | Placebo (n=1015) | Hazard Ratio (95% CI) | p-value (logrank)
CV death or heart failure hospitalization | 334 | 406 | 0.77; (0.67–0.89) | <0.001
CV death | 219 | 252 | 0.85; (0.71–1.02) | 0.072
Heart failure hospitalization | 207 | 286 | 0.68; (0.57–0.81) | <0.001

In CHARM–Added, 2548 subjects receiving an ACE inhibitor were randomized to ATACAND or placebo. The specific ACE inhibitor and dose were at the discretion of the investigators, who were encouraged to titrate patients to doses known to be effective in clinical outcome trials, subject to patient tolerability. Forced titration to maximum tolerated doses of ACE inhibitor was not required.

The mean age was 64 years and 21% were female, 24% were NYHA II, 73% were NYHA III, 3% were NYHA IV, and the mean ejection fraction was 28%. Fifty-six percent had a history of myocardial infarction, 48% had a history of hypertension, and 30% had diabetes. Concomitant drugs at baseline in addition to ACE inhibitors were diuretics (90%), digoxin (58%), beta-blockers (55%), and spironolactone (17%). The mean daily dose of ATACAND was approximately 24 mg and 61% of subjects on treatment received 32 mg once daily.

After a median follow-up of 41 months, there was a 15% reduction in the risk of cardiovascular death or heart failure hospitalization on ATACAND (p=0.011), with both components contributing to the overall effect (Table 2). There was no evident relationship between dose of ACE inhibitor and the benefit of ATACAND.

Table 2. CHARM — Added: Primary Endpoint and its Components
Endpoint (time to first event) | ATACAND (n=1276) | Placebo (n=1272) | Hazard Ratio (95% CI) | p-value (logrank)
CV death or heart failure hospitalization | 483 | 538 | 0.85 (0.75–0.96) | 0.011
CV death | 302 | 347 | 0.84 (0.72–0.98) | 0.029
Heart failure hospitalization | 309 | 356 | 0.83 (0.71–0.96) | 0.014

In these two studies, the benefit of ATACAND in reducing the risk of CV death or heart failure hospitalization (18% p<0.001) was evident in major subgroups (see Figure), and in patients on other combinations of cardiovascular and heart failure treatments, including ACE inhibitors and beta-blockers.

Figure. CV Death or Heart Failure Hospitalization in Subgroups – LV Systolic Dysfunction Trials

16 HOW SUPPLIED/STORAGE AND HANDLING

No. 3782 — Tablets ATACAND, 4 mg, are white to off-white, circular/biconvex-shaped, non-film-coated scored tablets, coded ACF on one side and 004 on the other. They are supplied as follows:

Bottles of 30 | NDC 54868-5591-0

No. 3780 — Tablets ATACAND, 8 mg, are light pink, circular/biconvex-shaped, non-film-coated scored tablets, coded ACG on one side and 008 on the other. They are supplied as follows:

Bottles of 30 | NDC 54868-5489-0

No. 3781 — Tablets ATACAND, 16 mg, are pink, circular/biconvex-shaped, non-film-coated scored tablets, coded ACH on one side and 016 on the other. They are supplied as follows:

Bottles of 30 | NDC 54868-4413-0

No. 3791 — Tablets ATACAND, 32 mg, are pink, circular/biconvex-shaped, non-film-coated scored tablets, coded ACL on one side and 032 on the other. They are supplied as follows:

Bottles of 30 | NDC 54868-4612-0

Storage

Store at 25°C (77°F); excursions permitted to 15-30°C (59-86°F) [see USP Controlled Room Temperature].Keep container tightly closed.

17 PATIENT COUNSELING INFORMATION

Pregnancy – Female patients of childbearing age should be told about the consequences of second- and third-trimester exposure to drugs that act on the renin-angiotensin system, and they should also be told that these consequences do not appear to have resulted from intrauterine drug exposure that has been limited to the first trimester. These patients should be asked to report pregnancies to their physicians as soon as possible.

Post-menarche adolescents should be questioned on a regular basis as to changes in menstrual pattern and the possibility of pregnancy.

Manufactured under the license

from Takeda Pharmaceutical Company, Ltd.

by: AstraZeneca AB, S-151 85 Södertälje, Sweden

for: AstraZeneca LP, Wilmington, DE 19850

ATACAND is a trademark of the AstraZeneca group of companies.

Rev. 04/11

©AstraZeneca 2009

Relabeling and Repackaging by:
Physicians Total Care, Inc.
Tulsa, Oklahoma 74146